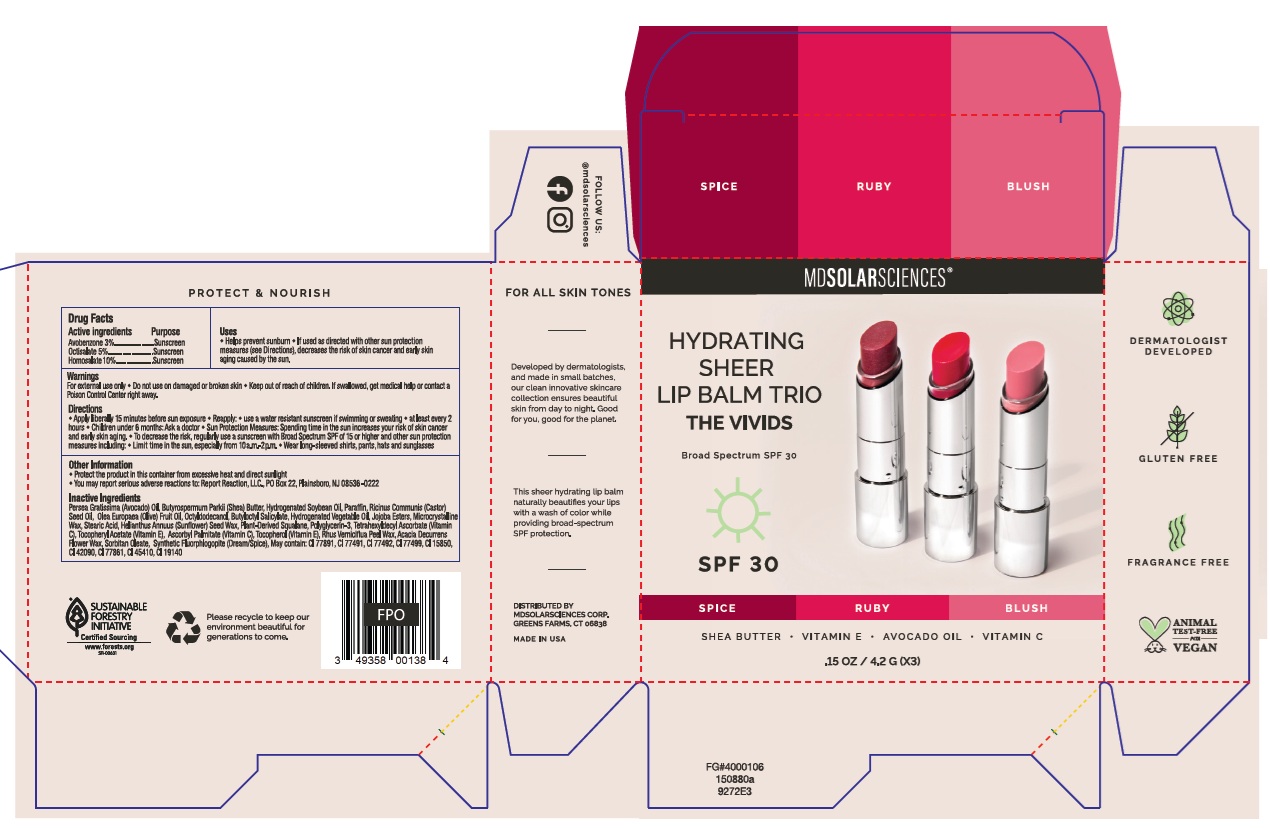 DRUG LABEL: Hydrating Sheer Lip Balm Trio The Vivids
NDC: 49358-006 | Form: KIT | Route: TOPICAL
Manufacturer: MDSolarSciences
Category: otc | Type: HUMAN OTC DRUG LABEL
Date: 20250611

ACTIVE INGREDIENTS: OCTISALATE 50 mg/1 g; AVOBENZONE 30 mg/1 g; HOMOSALATE 100 mg/1 g; OCTISALATE 50 mg/1 g; AVOBENZONE 30 mg/1 g; HOMOSALATE 100 mg/1 g; OCTISALATE 50 mg/1 g; AVOBENZONE 30 mg/1 g; HOMOSALATE 100 mg/1 g
INACTIVE INGREDIENTS: ALPHA-TOCOPHEROL ACETATE; CI 77491; CI 77492; CI 42090; JOJOBA OIL, RANDOMIZED; SHEA BUTTER; SORBITAN OLEATE; CI 19140; OCTYLDODECANOL; CI 77499; CI 15850; TETRAHEXYLDECYL ASCORBATE; PARAFFIN; CI 77891; AVOCADO OIL; CASTOR OIL; MICROCRYSTALLINE WAX; STEARIC ACID; HELIANTHUS ANNUUS (SUNFLOWER) SEED WAX; RHUS VERNICIFLUA PEEL WAX; OLIVE OIL; ASCORBYL PALMITATE; CI 45410; SQUALANE; POLYGLYCERIN-3; TOCOPHEROL; BUTYLOCTYL SALICYLATE; HYDROGENATED SOYBEAN OIL; ACACIA DECURRENS FLOWER WAX; ALPHA-TOCOPHEROL ACETATE; CI 77491; CI 77492; CI 42090; JOJOBA OIL, RANDOMIZED; SHEA BUTTER; CI 19140; OCTYLDODECANOL; CI 77499; CI 15850; TETRAHEXYLDECYL ASCORBATE; CI 77891; AVOCADO OIL; CASTOR OIL; MICROCRYSTALLINE WAX; STEARIC ACID; HELIANTHUS ANNUUS (SUNFLOWER) SEED WAX; RHUS VERNICIFLUA PEEL WAX; OLIVE OIL; ASCORBYL PALMITATE; CI 45410; SQUALANE; POLYGLYCERIN-3; TOCOPHEROL; BUTYLOCTYL SALICYLATE; HYDROGENATED SOYBEAN OIL; ACACIA DECURRENS FLOWER WAX; SORBITAN OLEATE; PARAFFIN; ALPHA-TOCOPHEROL ACETATE; CI 77491; CI 77492; CI 42090; JOJOBA OIL, RANDOMIZED; SHEA BUTTER; CI 19140; OCTYLDODECANOL; CI 77499; CI 15850; TETRAHEXYLDECYL ASCORBATE; CI 77891; AVOCADO OIL; CASTOR OIL; MICROCRYSTALLINE WAX; STEARIC ACID; HELIANTHUS ANNUUS (SUNFLOWER) SEED WAX; RHUS VERNICIFLUA PEEL WAX; OLIVE OIL; ASCORBYL PALMITATE; CI 45410; SQUALANE; POLYGLYCERIN-3; TOCOPHEROL; BUTYLOCTYL SALICYLATE; HYDROGENATED SOYBEAN OIL; ACACIA DECURRENS FLOWER WAX; SORBITAN OLEATE; MAGNESIUM POTASSIUM ALUMINOSILICATE FLUORIDE; PARAFFIN

Hydrating Sheer Lip Balm Trio The Vivids

Drug Facts

ACTIVE INGREDIENT

Active ingredients | Purpose
Avobenzone 3% | Sunscreen
Octisalate 5% | Sunscreen
Homosalate 10% | Sunscreen

Uses

- Helps prevent sunburn
- If used as directed with other sun protection measures (see Directions), decreases the risk of skin cancer and early skin aging caused by the sun.

Warnings

For external use only

- Do not use on damaged or broken skin

- Keep out of reach of children. If swallowed, get medical help or contact a Poison Control Center right away.

Directions

- Apply liberally 15 minutes before sun exposure
- Reapply:
  - use a water resistant sunscreen if swimming or sweating
  - at least every 2 hours
- Children under 6 months: Ask a doctor
- Sun Protection Measures :Spending time in the sun increases your risk of skin cancer and early skin aging.
  To decrease the risk, regularly use a sunscreen with Broad Spectrum SPF of 15 or higher and other sun protection measures including:
  - Limit time in the sun, especially from 10a.m.- 2p.m.
  - Wear long-sleeved shirts, pants, hats and sunglasses

Other Information

- Protect the product in this container from excessive heat and direct sunlight
- You may report serious adverse reactions to: Report Reaction, LLC., PO Box 22, Plainsboro, NJ 08536-0222

Inactive Ingredients

Persea Gratissima (Avocado) Oil, Butyrospermum Parkii (Shea) Butter, Hydrogenated Soybean Oil, Paraffin, Ricinus Communis (Castor) Seed Oil, Olea Europaea (Olive) Fruit Oil, Octyldodecanol, Butyloctyl Salicylate, Hydrogenated Vegetable Oil, Jojoba Esters, Microcrystalline Wax, Stearic Acid, Helianthus Annuus (Sunflower) Seed Wax, Plant-Derived Squalane, Polyglycerin-3, Tetrahexyldecyl Ascorbate (Vitamin C), Tocopheryl Acetate (Vitamin E), Ascorbyl Palmitate (Vitamin C), Tocopherol (Vitamin E), Rhus Verniciflua Peel Wax, Acacia Decurrens Flower Wax, Sorbitan Oleate, Synthetic Fluorphlogopite (Dream/Spice), May contain: CI 77891, CI 77491, CI 77492, CI 77499, CI 15850, CI 42090, CI 77861, CI 45410, CI 19140

Company Information

DISTRIBUTED BY
MDSOLARSCIENCES CORP.
GREENS FARMS, CT 06838